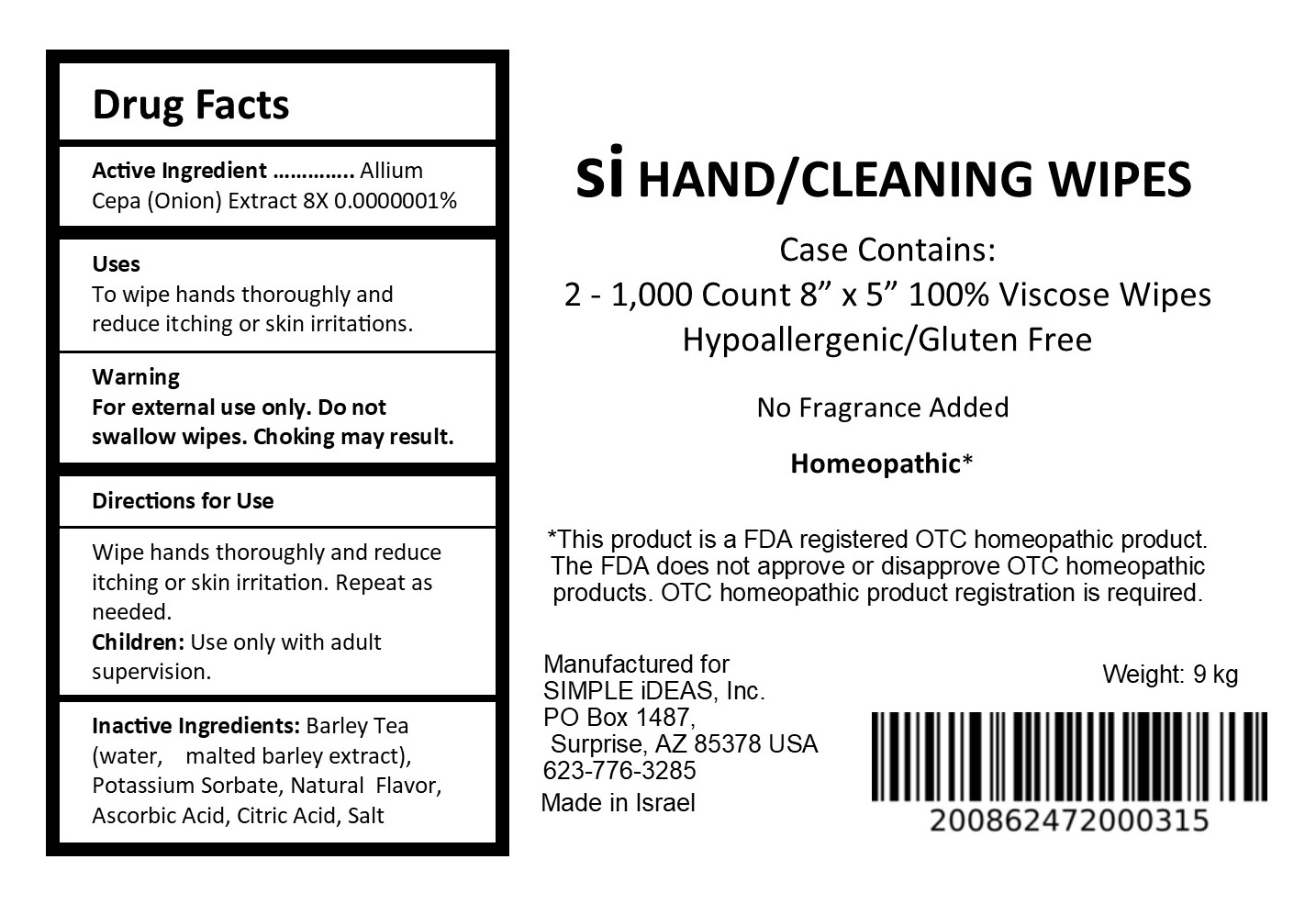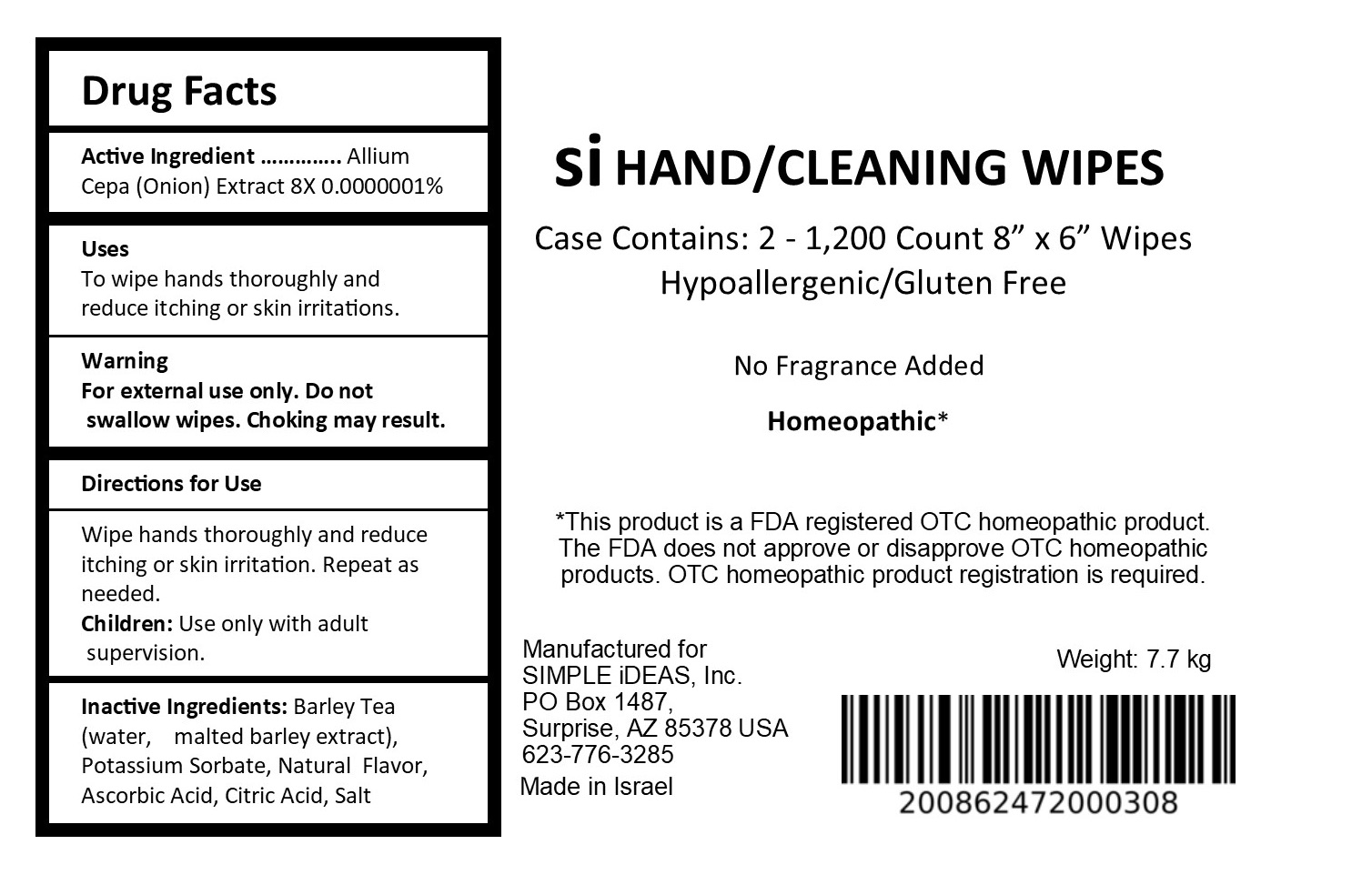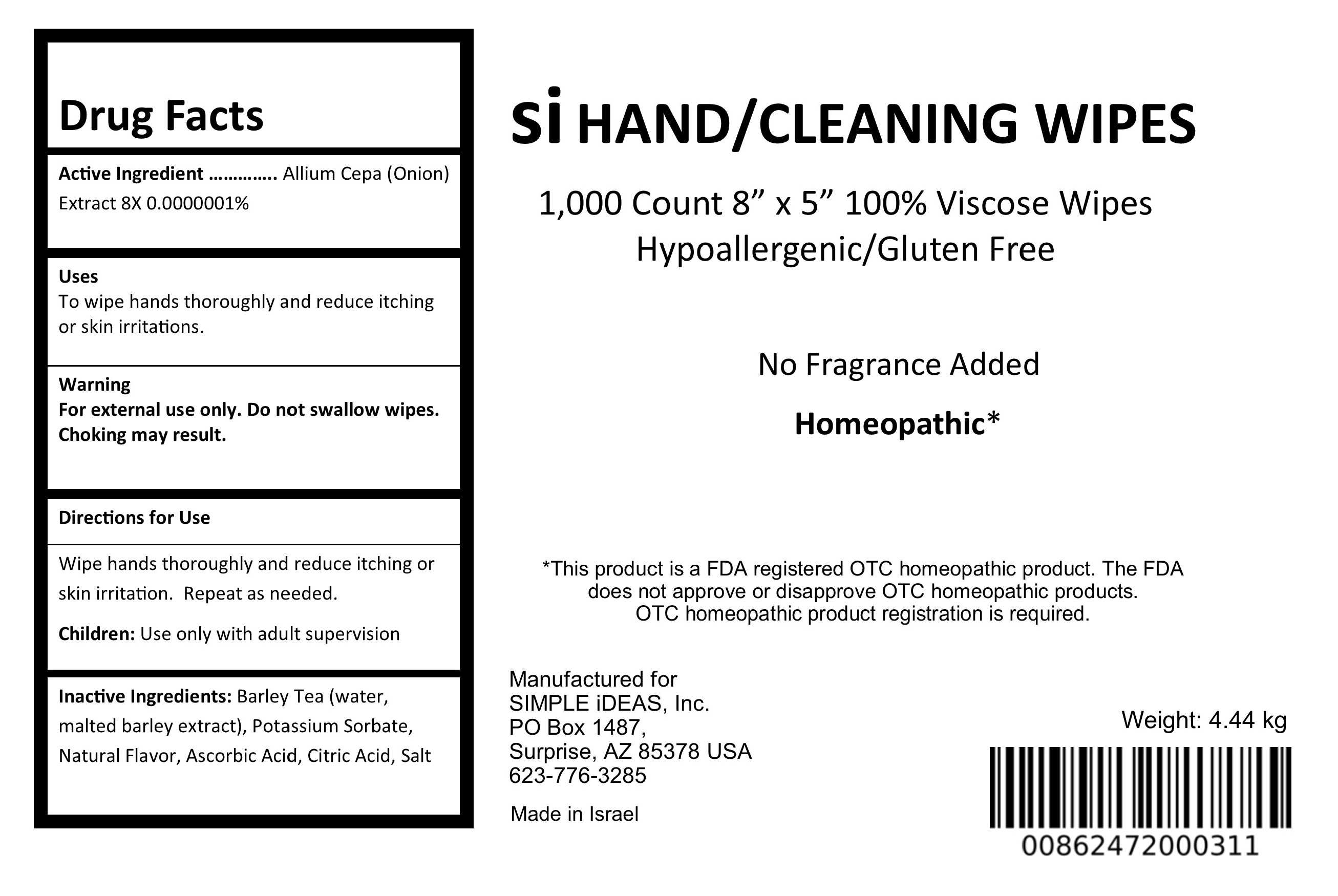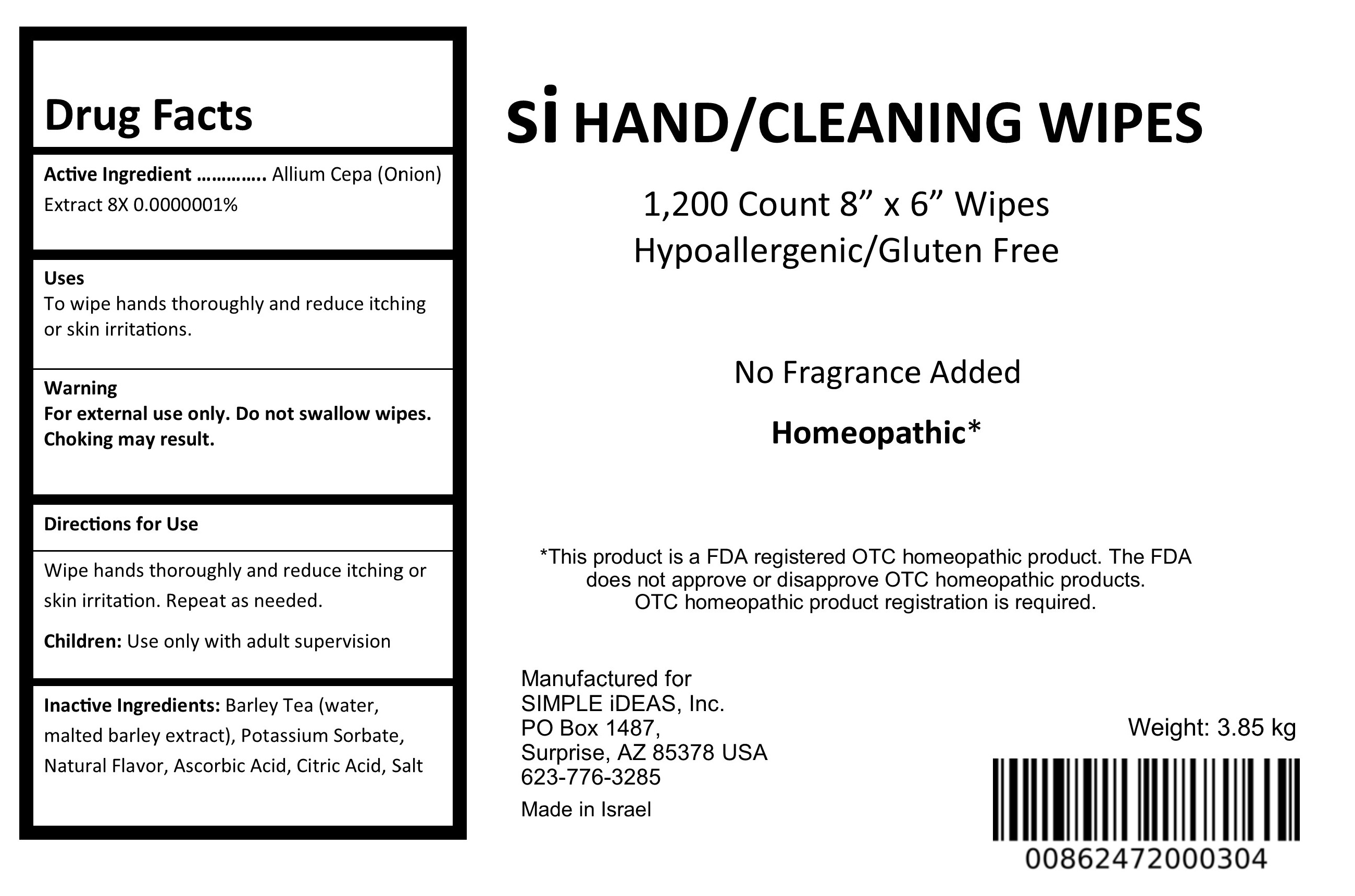 DRUG LABEL: Viscose Wipes
NDC: 71041-1601 | Form: CLOTH
Manufacturer: SIMPLE iDEAS, Inc.
Category: homeopathic | Type: HUMAN OTC DRUG LABEL
Date: 20181003

ACTIVE INGREDIENTS: ONION 8 [hp_X]/1 1
INACTIVE INGREDIENTS: POTASSIUM SORBATE; ASCORBIC ACID; CITRIC ACID MONOHYDRATE; SODIUM CHLORIDE; BARLEY

Si Hand Cleaning Wipes Homeopathic

ACTIVE INGREDIENT

Allium Cepa 8x

INACTIVE INGREDIENT

Barley Tea Extract (water, malted barley extract), Potassium Sorbate, Natural Flavor, Ascorbic Acid, Citric Acid, Salt

PURPOSE

To wipe hands thoroughly and reduce itching or skin irritations.

WARNINGS

For external use only.

Do not swallow wipes. Choking may result.

Keep out of reach of children.

DOSAGE AND ADMINISTRATION

To wipe hands thoroughly and reduce itching or skin irritations. Repeat as needed.

Children: Use only with adult supervision.

INDICATIONS AND USAGE

To wipe hands thoroughly and reduce itching or skin irritations. Repeat as needed.

Children: Use only with adult supervision.